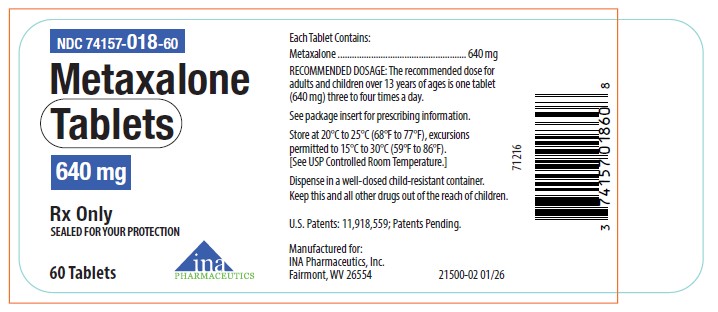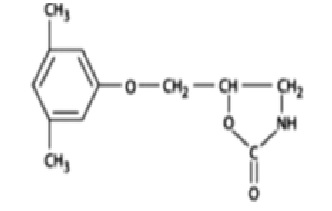 DRUG LABEL: Metaxalone
NDC: 74157-018 | Form: TABLET
Manufacturer: INA Pharmaceutics Inc
Category: prescription | Type: HUMAN PRESCRIPTION DRUG LABEL
Date: 20260203

ACTIVE INGREDIENTS: METAXALONE 640 mg/1 1
INACTIVE INGREDIENTS: ALGINIC ACID; FD&C YELLOW NO. 6; LACTOSE MONOHYDRATE; MAGNESIUM STEARATE; POVIDONE; PROPYLENE GLYCOL ALGINATE

HIGHLIGHTS OF PRESCRIBING INFORMATION

These highlights do not include all the information needed to use METAXALONE TABLETS, 640 mg, safely and effectively. See full prescribing information for METAXALONE TABLETS, 640 mg.
METAXALONE tablets, for oral use
Initial U.S. Approval: 1962

1 INDICATIONS AND USAGE

Metaxalone Tablets, 640 mg, is a muscle relaxant, indicated as an adjunct to rest, physical therapy, and other measures for the relief of discomforts associated with acute, painful musculoskeletal conditions in adult and pediatric patients 13 years of age and older. (1)

2 DOSAGE AND ADMINISTRATION

- Recommended dosage in adults and pediatric patients 13 years of age and older is 640 mg taken orally, with or without food, three to four times a day (2)
- Maximum recommended daily dosage is 2,560 mg (one tablet four times a day) (2)
- Metaxalone Tablets 640 mg and SKELAXIN 800 mg tablets are not mutually substitutable on a mg-to-mg basis due to differences in pharmacokinetic profiles (5.3, 12.3). When it is appropriate to switch a patient taking SKELAXIN 800 mg on an empty stomach to Metaxalone Tablets, 640 mg (2):
  - Stop SKELAXIN 800 mg threetimes a day and start Metaxalone Tablets 640 mg threetimes a day on an empty stomach OR
  - Stop SKELAXIN 800 mg fourtimes a day and start Metaxalone Tablets 640 mg fourtimes a day on an empty stomach.
- For patients who have been taking either product with food, do not switch between SKELAXIN 800 mg and Metaxalone Tablets, 640 mg (2).

3 DOSAGE FORMS AND STRENGTHS

Tablets: 640 mg. (3)

4 CONTRAINDICATIONS

• Known hypersensitivity to any components of this product. (4)
• Known tendency to drug induced, hemolytic, or other anemias. (4)
• Severe renal or hepatic impairment. (4)

5 WARNINGS AND PRECAUTIONS

- Serotonin Syndrome: Cases of serotonin syndrome, a potentially life-threatening condition, have been reported during concomitant use of metaxalone (within the recommended dosage range) and other serotonergic drugs and with the use of metaxalone as the only serotonergic drug taken at a dosage higher than the recommended dosage. If concomitant use with another serotonergic drug is warranted, carefully observe the patient, particularly during treatment initiation and dosage increases. Discontinue Metaxalone Tablets, 640 mg if serotonin syndrome is suspected or it occurs. (5.1, 7.1)
- Central Nervous System (CNS) Depression: Metaxalone Tablets, 640 mg may impair mental and/or physical abilities required for the performance of hazardous tasks, such as operating machinery or driving a motor vehicle, and may enhance the effects of other CNS depressants including alcohol. Follow patients closely for signs and symptoms of respiratory depression and sedation. If concomitant use with another CNS depressant is warranted, closely monitor for signs of respiratory depression and sedation, particularly during treatment initiation and dosage increases. (5.2, 7.2)
- Risk with Inappropriate Switching to Metaxalone Tablets, 640 mg Inappropriate switching on a mg-to-mg basis from SKELAXIN (metaxalone) tablets, 800 mg to Metaxalone Tablets, 640 mg to achieve the same total daily metaxalone dosage may result in a clinically significant increase in metaxalone exposure which may increase the risk of metaxalone-associated adverse reactions including CNS depression. Metaxalone Tablets, 640 mg and SKELAXIN (metaxalone) tablets, 800 mg are not mutually substitutable on a mg-to-mg basis (5.3, 12.3).

6 ADVERSE REACTIONS

The most common adverse reactions to Metaxalone Tablets, 640 mg include drowsiness, dizziness, headache, and nervousness or “irritability”, nausea, vomiting, gastrointestinal upset. (6)

To report SUSPECTED ADVERSE REACTIONS, contact INA Pharmaceutics, Inc. at 1-866-835-0469 or FDA at 1-800-FDA-1088 or www.fda.gov/medwatch.

8 USE IN SPECIFIC POPULATIONS

- Geriatric Use: Geriatric patients may be especially susceptible to CNS depression associated with Metaxalone Tablets, 640 mg use. (8.5)
- Hepatic Impairment: Consider additional monitoring in patients with mild to moderate hepatic impairment. (4, 8.6)
- Renal impairment: Consider additional monitoring in patients with mild to moderate renal impairment (4, 8.7)

FULL PRESCRIBING INFORMATION

1 INDICATIONS AND USAGE

Metaxalone Tablets, 640 mg, are indicated as an adjunct to rest, physical therapy, and other measures for the relief of discomforts associated with acute, painful musculoskeletal conditions in adults and pediatric patients 13 years of age and older.

2 DOSAGE AND ADMINISTRATION

The recommended dosage of Metaxalone Tablets, 640 mg in adults and pediatric patients 13 years of age and older is 640 mg taken orally with or without food, three to four times a day. The maximum recommended daily dosage is 2,560 mg (one tablet four times a day).

Metaxalone Tablets, 640 mg and SKELAXIN 800 mg are not mutually substitutable on a mg-to-mg basis due to differences in pharmacokinetic profiles [see Warnings and Precautions (5.3)and Clinical Pharmacology (12.3)]. When it is appropriate to switch a patient taking SKELAXIN 800 mg on an empty stomach to Metaxalone Tablets, 640 mg:

- Stop SKELAXIN 800 mg threetimes a day and start Metaxalone Tablets 640 mg threetimes a day on an empty stomach, OR
- Stop SKELAXIN 800 mg fourtimes a day and start Metaxalone Tablets 640 mg fourtimes a day on an empty stomach.

For patients who have been taking either product with food, do not switch between SKELAXIN 800 mg and Metaxalone Tablets, 640 mg.

3 DOSAGE FORMS AND STRENGTHS

Tablets: 640 mg oval, peach-colored, debossed with M640 on one side and without markings on the other side.

4 CONTRAINDICATIONS

The use of Metaxalone Tablets, 640 mg is contraindicated in patients with:

- Known hypersensitivity to any components of this product.
- Known tendency for drug-induced, hemolytic, or other anemias.
- Severe renal or hepatic impairment.

5 WARNINGS AND PRECAUTIONS

5.1 Serotonin Syndrome

Cases of serotonin syndrome, a potentially life-threatening condition, have been reported during concomitant use of metaxalone (within the recommended dosage range) and other serotonergic drugs [see Drug Interactions (7)] and with the use of metaxalone as the only serotonergic drug taken at a dosage higher than the recommended dosage [see Overdosage (10)] . Serotonergic drugs include selective serotonin reuptake inhibitors (SSRIs), serotonin and norepinephrine reuptake inhibitors (SNRIs), tricyclic antidepressants (TCAs), triptans, 5-HT3 receptor antagonists, opioids (particularly fentanyl, meperidine, and methadone), drugs that affect the serotonergic neurotransmitter system (e.g., mirtazapine, trazodone, tramadol), and drugs that impair metabolism of serotonin (including monoamine oxidase (MAO) inhibitors, both those intended to treat psychiatric disorders and also others, such as linezolid and intravenous methylene blue) [see Drug Interactions (7.2)] .

Serotonin syndrome symptoms may include mental status changes (e.g., agitation, hallucinations, coma), autonomic instability (e.g., tachycardia, labile blood pressure, hyperthermia), neuromuscular aberrations (e.g., hyperreflexia, incoordination, rigidity), and/or gastrointestinal symptoms (e.g., nausea, vomiting, diarrhea). The onset of symptoms generally occurs within several hours to a few days after initiation of a serotonergic drug but may occur later than that.

If concomitant use of Metaxalone Tablets, 640 mg and another serotonergic drug is warranted, reassess the patient, particularly during treatment initiation and dosage modification. Discontinue Metaxalone Tablets, 640 mg if serotonin syndrome is suspected or occurs.

5.2 Central Nervous System Depression

Because of central nervous system (CNS) depressant effects, metaxalone may impair mental and/or physical abilities required for performance of hazardous tasks, such as operating machinery or driving a motor vehicle, especially when used with other CNS depressants including alcohol. Geriatric patients may be especially susceptible to CNS depression associated with metaxalone use. When used concomitantly, the sedative effects of metaxalone and other CNS depressants (e.g., alcohol, benzodiazepines, opioids, tricyclic antidepressants) may be additive [see Drug Interactions (7)].

Follow patients treated with Metaxalone Tablets, 640 mg closely for signs and symptoms of respiratory depression and sedation. If concomitant use of metaxalone and another CNS depressant is warranted, closely monitor for signs of respiratory depression and sedation, particularly during treatment initiation and dosage increases.

5.3 Risk with Inappropriate Switching to Metaxalone Tablets, 640 mg

Inappropriate switching on a mg-to-mg basis from SKELAXIN (metaxalone) tablets, 800 mg to Metaxalone Tablets, 640 mg to achieve the same total daily metaxalone dosage may result in a clinically significant increase in metaxalone exposure which may increase the risk of metaxalone-associated adverse reactions including CNS depression. For example, it is inappropriate to switch from four SKELAXIN 800 mg tablets (3,200 mg) per day to five tablets of Metaxalone Tablets, 640 mg (3,200 mg) per day [1.25 times the maximum recommended daily dosage of 2,560 mg] [see Dosage and Administration (2)]. Metaxalone Tablets 640 mg and SKELAXIN (metaxalone) tablets, 800 mg are not mutually substitutable on a mg-to-mg basis [see Clinical Pharmacology (12.3)] .

It is generally inappropriate to switch between Metaxalone Tablets, 640 mg and SKELAXIN 800 mg to mediate metaxalone-associated adverse reactions.

For recommendations on how to switch from SKELAXIN (metaxalone) tablets, 800 mg, to Metaxalone Tablets, 640 mg, see Dosage and Administration (2).

6 ADVERSE REACTIONS

The following adverse reactions associated with the use of metaxalone were identified in clinical studies or postmarketing reports. Because some of these reactions were reported voluntarily from a population of uncertain size, it is not always possible to reliably estimate their frequency or establish a causal relationship to drug exposure. The most frequent reactions to metaxalone were:

- CNS: drowsiness, dizziness, headache, and nervousness or “irritability”
- Digestive: nausea, vomiting, gastrointestinal upset.

Other adverse reactions were:

- Allergic: anaphylaxis have been reported with metaxalone.
- CNS: cases of serotonin syndrome, a potentially life-threatening condition, have been reported during concomitant use of metaxalone (within the recommended dosage range) and other serotonergic drugs and with the use of metaxalone as the only serotonergic drug taken at a dosage higher than the recommended dosage [see Warnings and Precautions (5.1), Drug Interactions (7.2), and Overdosage (10)].
- Hematologic: leucopenia; hemolytic anemia.
- Hepatobiliary: jaundice.
- Immune System: hypersensitivity reaction, rash with or without pruritus.

7 DRUG INTERACTIONS

7.1 Serotonergic Drugs

If concomitant use of Metaxalone Tablets, 640 mg and another serotonergic drug is warranted, carefully observe the patient, particularly during treatment initiation and dosage modification. Discontinue Metaxalone Tablets, 640 mg if serotonin syndrome is suspected or if it occurs.

Serotonin syndrome has resulted from concomitant use of metaxalone (within the recommended dosage range) and other serotonergic drugs [see Warnings and Precautions (5.1)].

Serotonergic drugs include selective serotonin reuptake inhibitors (SSRIs), serotonin and norepinephrine reuptake inhibitors (SNRIs), tricyclic antidepressants (TCAs), triptans, 5-HT3 receptor antagonists, opioids (particularly fentanyl, meperidine, and methadone), drugs that affect the serotonin neurotransmitter system (e.g., mirtazapine, trazodone, tramadol), monoamine oxidase (MAO) inhibitors (those intended to treat psychiatric disorders and also others, such as linezolid and intravenous methylene blue).

7.2 Depressants

If concomitant use of Metaxalone Tablets, 640 mg and another CNS depressant is warranted, closely monitor for signs of respiratory depression and sedation, particularly during treatment initiation and dosage modification.

Due to the additive pharmacologic effect, concomitant use of Metaxalone Tablets, 640 mg with other CNS depressants may increase the risk of sedation and respiratory depression [see Warnings and Precautions (5.2)].

7.3 Interaction of Metaxalone with Benedict’s Tests

False-positive Benedict's tests, due to an unknown reducing substance, have been noted in metaxalone-treated patients. A glucose-specific test will differentiate findings.

8 USE IN SPECIFIC POPULATIONS

8.1 Pregnancy

Risk Summary

There are no available data on metaxalone use in pregnancy to evaluate for a drug-associated risk of major birth defects, miscarriage or other adverse maternal or fetal outcomes despite decades of metaxalone use. Reproduction studies in rats have not revealed evidence of impaired fertility or harm to fetus due to metaxalone.

The estimated background risk of major birth defects and miscarriage for the indicated population is unknown. All pregnancies have a background risk of birth defect, loss, or other adverse outcomes. In the U.S. general population, the estimated risk of major birth defects and miscarriage in clinically recognized pregnancies is 2% to 4% and 15% to 20%, respectively.

8.2 Lactation

Risk Summary

There are no data on the presence of metaxalone or its metabolite in either human or animal milk, the effects on the breastfed infant, or the effects on milk production. The developmental and health benefits of breastfeeding should be considered along with the mother’s clinical need for metaxalone and any potential adverse effects on the breastfed infant from metaxalone or from the underlying maternal condition.

8.4 Pediatric Use

Metaxalone Tablets, 640 mg are indicated as an adjunct to rest, physical therapy, and other measures for the relief of discomforts associated with acute, painful musculoskeletal conditions in pediatric patients 13 years of age and older.

The safety and effectiveness of Metaxalone Tablets, 640 mg in pediatric patients less than 13 years of age have not been established.

8.5 Geriatric Use

Clinical studies of Metaxalone Tablets, 640 mg did not include sufficient numbers of patients 65 years of age and older to determine whether they respond differently from younger adult patients. The effects of age on the pharmacokinetics of Metaxalone Tablets, 640 mg have not been evaluated. Geriatric patients may be especially susceptible to CNS depression associated with metaxalone use [see Warnings and Precautions (5.2)].

8.6 Hepatic Impairment

Metaxalone Tablets. 640 mg are contraindicated in patients with severe hepatic impairment . Metaxalone Tablets, 640 mg should be used with caution and additional monitoring should be considered in patients with mild to moderate hepatic impairment. The effect of hepatic impairment on metaxalone pharmacokinetics is unknown; however, metaxalone undergoes extensive hepatic metabolism [see Clinical Pharmacology (12.3)] .

8.7 Renal Impairment

Metaxalone Tablets, 640 mg are contraindicated in patients with severe renal impairment . Metaxalone Tablets, 640 mg should be used with caution and additional monitoring should be considered in patients with mild to moderate renal impairment. The effect of renal impairment on metaxalone pharmacokinetics is unknown; however, metaxalone undergoes renal excretion as unidentified metabolites [see Clinical Pharmacology (12.3)] .

10 OVERDOSAGE

Clinical Presentations of Metaxalone Overdose

Cardiovascular effects may include tachycardia and hypertension; hypotension has also been reported. CNS manifestations may include CNS depression, agitation, hallucinations, delusions, seizures, respiratory depression, and coma. Deaths by deliberate or accidental overdose may occur with metaxalone, particularly in combination with other CNS depressants (including alcohol). Serotonin syndrome, leading to muscle rigidity, tremor, and hyperthermia, has been reported [see Warnings and Precautions (5.1), Drug Interactions (7.1, 7.2)].

Treatment of Overdose

The standard of treatment is supportive care. Monitor for CNS and respiratory depression and, manage airway with oxygen as needed. Gastrointestinal decontamination procedures (including emesis) should generally be avoided because aspiration may result from CNS depression and seizures. Extracorporeal elimination such as hemodialysis or plasmapheresis have no proven clinical benefit.

Consider contacting the Poison Help line (1-800-222-1222) or a medical toxicologist for additional overdose management recommendations.

11 DESCRIPTION

Metaxalone Tablets, 640 mg for oral administration, are available as 640 mg oval, peach-colored tablets, debossed with M640 on one side and no markings on the other side. Each tablet contains 640 mg metaxalone, a muscle relaxant, and the following inactive ingredients: alginic acid, FD&C yellow #6, lactose monohydrate, magnesium stearate, propylene glycol alginate and povidone.

Chemically, metaxalone is 5-[(3, 5- dimethylphenoxy) methyl]-2-oxazolidinone. The empirical formula is C12H15NO3, which corresponds to a molecular weight of 221.25. The structural formula is:

Metaxalone is a white to almost white, odorless crystalline powder freely soluble in chloroform, soluble in methanol and in 96% ethanol, but practically insoluble in ether or water.

12 CLINICAL PHARMACOLOGY

12.1 Mechanism of Action

The mechanism of action of metaxalone as an adjunct to rest, physical therapy, and other measures for the relief of discomfort associated with acute, painful musculoskeletal conditions has not been established, but may be due to general CNS depression. Metaxalone has no direct action on the contractile mechanism of striated muscle, the motor end plate, or the nerve fiber.

12.2 Pharmacodynamics

The exposure-response relationship and time course of pharmacodynamic response for the safety and effectiveness of metaxalone not been fully characterized.

12.3 Pharmacokinetics

Absorption

In a relative bioavailability study in healthy adult volunteers, the Cmax (peak plasma concentration) and AUC (extent of absorption) values of metaxalone from Metaxalone Tablets, 640 mg were found to be similar to those from SKELAXIN 800 mg tablets. After a single dose of Metaxalone Tablets, 640 mg, under fasted conditions, mean Cmax and AUC values were 2 mcg/mL and 16 mcg*h/mL, respectively. The time-to-peak plasma concentration (Tmax) occurred at 3.5 hours (range 1.5-12 hours). The plasma half-life in adult healthy subjects was approximately 5 hours after administration of Metaxalone Tablets, 640 mg.

Effect of Food: Table 1 displays the effect of a high fat meal on the pharmacokinetics of metaxalone.

Table 1: Effect of a High Fat Meal on the Pharmacokinetics of Metaxalone
Metaxalone Product | Cmax^1 | AUC0-t^1 | AUC0-inf^1 | Tmax^2
Metaxalone Tablets, 640 mg | 23% Increase | 7% Increase | 6% Increase | 8 hours (3.5-24 hours)
SKELAXIN (metaxalone) tablets, 800 mg | 76% Increase | 32% Increase | 32% Increase | 5 hours (2.5-24 hours)

1= Presented as ratio fed/fasted groups. Fed group received a high fat meal.
2= Presented as median (range) under fed state.

Distribution

For Metaxalone Tablets, 640 mg, the metaxalone apparent volume of distribution (V/F) was approximately 800 Liters. Metaxalone plasma protein binding is unknown.

Elimination

For Metaxalone Tablets, 640 mg, the metaxalone plasma half-life was approximately 5 hours.

Metabolism: Metaxalone is metabolized by the liver. CYP1A2, CYP2D6, CYP2E1, and CYP3A4 and, to a lesser extent, CYP2C8, CYP2C9, and CYP2C19 are involved in metaxalone metabolism.

Excretion: Metaxalone is excreted in the urine as unidentified metabolites.

Specific Populations

For Metaxalone Tablets, 640 mg, the effect of age, renal impairment, and hepatic impairment on the pharmacokinetics of metaxalone is unknown.

Males and Females:The metaxalone Cmax increased by 36% and AUC inf by 31%, in females compared to males following administration of 640 mg of Metaxalone Tablets. These data were not adjusted for other factors (e.g., weight, renal function). The clinical significance of these findings is unknown.

Drug Interaction Studies

In Vitro Studies: Metaxalone does not inhibit CYP1A2, CYP2A6, CYP2B6, CYP2C8, CYP2C9, CYP2C19, CYP2D6, CYP2E1, and CYP3A4 or induce CYP1A2, CYP2B6, and CYP3A4.

13 NONCLINICAL TOXICOLOGY

13.1 Carcinogenesis, Mutagenesis, Impairment of Fertility

Carcinogenesis

Long-term studies to evaluate the carcinogenic potential of metaxalone have not been conducted.

Mutagenesis

Studies to evaluate the mutagenic potential of metaxalone have not been conducted.

Impairment of Fertility

Reproduction studies in rats have not revealed evidence of impaired fertility or harm to the fetus due to metaxalone.

16 HOW SUPPLIED/STORAGE AND HANDLING

Metaxalone Tablets, 640 mg are available as oval, peach-colored tablets, debossed with M640 on one side and no markings on the other side. Metaxalone Tablets, 640 mg are packaged as a bottle of 60 tablets, NDC 74157-018-60

Store at 20°C to 25°C (68°F to 77°F), excursions permitted to 15°C to 30°C (59°F to 86°F). [see USP Controlled Room Temperature].

17 PATIENT COUNSELING INFORMATION

Serotonin Syndrome

Inform patients that Metaxalone Tablets, 640 mg could cause a rare but potentially life-threatening condition called serotonin syndrome. Warn patients of the symptoms of serotonin syndrome and to seek medical attention right away if symptoms develop. Instruct patients to inform their healthcare providers if they are taking, or plan to take, serotonergic drugs [see Warnings and Precautions (5.1) and Drug Interactions (7.1)] .

Central Nervous System Depression

Advise patients that Metaxalone Tablets, 640 mg may impair mental and/or physical abilities required for performance of hazardous tasks, such as operating machinery or driving a motor vehicle, especially when used with alcohol and other CNS depressants [see Drug Interactions (7.2)] .

Manufactured for: INA Pharmaceutics, Inc., Fairmont, WV 26554
U.S. Patents: 11,918,559; Patents Pending
21507-03 01/26
1274E##

Product label

NDC 74157-018-60

Metaxalone Tablets

640 mg

Rx Only

SEALED FOR YOUR PROTECTION

60 Tablets